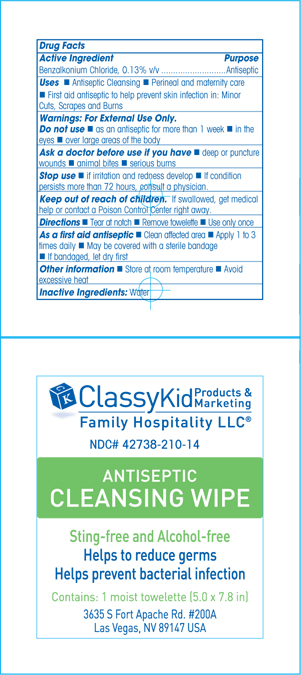 DRUG LABEL: BZK Cleansing
NDC: 42738-210 | Form: SWAB
Manufacturer: Family Hospitality LLC
Category: otc | Type: HUMAN OTC DRUG LABEL
Date: 20120517

ACTIVE INGREDIENTS: BENZALKONIUM CHLORIDE 1 mL/750 mL
INACTIVE INGREDIENTS: WATER

Cleansing towelette

Active Ingredient Purpose

Benzalkonium Chloride 0.13% v/v Antiseptic

Use: Cleansing towelette

- First aid antiseptic to help prevent skin infection in minor cuts, scrapes and burns
- Antiseptic cleansing
- Perineal and maternity care

Warnings

For external use only

Indications and Usage

General antiseptic
Ask a doctor before use if you have

- deep or puncture wounds
- animal bites
- serious burns

Stop use if

- irritation and redness develop
- if condition persists for more than 72 hours, consult a physician.

Directions

- Tear at notch, remove towelette, use only once

As a first aid antiseptic

- clean affeected area
- apply 1 to 3 times daily
- may be covered with a sterile bandage
- if bandaged let dry first

Keep out of reach of children

If swallowed, get medical help or contact a Poison Control Center right away.

Do not use

- as a first aid antiseptic for more than 1 week
- in the eyes
- over large areas of the body

Inactive ingredient section

Inactive ingredient(s): water

Principal Display Panel

Cleansing towelette

Benzalkonium

CK_BZK.jpg